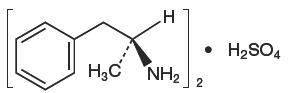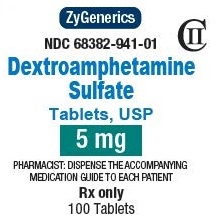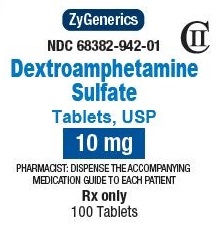 DRUG LABEL: DEXTROAMPHETAMINE SULFATE
NDC: 68382-941 | Form: TABLET
Manufacturer: Zydus Pharmaceuticals (USA) Inc. 
Category: prescription | Type: HUMAN PRESCRIPTION DRUG LABEL
Date: 20211217
DEA Schedule: CII

ACTIVE INGREDIENTS: DEXTROAMPHETAMINE SULFATE 5 mg/1 1
INACTIVE INGREDIENTS: CALCIUM SULFATE; SILICON DIOXIDE; SUCROSE; STARCH, CORN; MAGNESIUM STEARATE; CELLULOSE, MICROCRYSTALLINE; D&C YELLOW NO. 10; FD&C RED NO. 40

DEXTROAMPHETAMINE SULFATE - dextroamphetamine sulfate tablet

CII

Rx only

WARNING

AMPHETAMINES HAVE A HIGH POTENTIAL FOR ABUSE. ADMINISTRATION OF AMPHETAMINES FOR PROLONGED PERIODS OF TIME MAY LEAD TO DRUG DEPENDENCE AND MUST BE AVOIDED. PARTICULAR ATTENTION SHOULD BE PAID TO THE POSSIBILITY OF SUBJECTS OBTAINING AMPHETAMINES FOR NON-THERAPEUTIC USE OR DISTRIBUTION TO OTHERS, AND THE DRUGS SHOULD BE PRESCRIBED OR DISPENSED SPARINGLY.

MISUSE OF AMPHETAMINES MAY CAUSE SUDDEN DEATH AND SERIOUS CARDIOVASCULAR ADVERSE EVENTS.

DESCRIPTION

Dextroamphetamine sulfate, USP is the dextro isomer of the compound d,l-amphetamine sulfate, a sympathomimetic amine of the amphetamine group. Chemically, dextroamphetamine is d-alpha-methylphenethylamine, and is present in all forms of dextroamphetamine sulfate, USP as the neutral sulfate. The structural formula is as follows:

(C9H13N)2∙H2SO4 M.W. 368.49

Inactive Ingredients

Calcium sulfate, colloidal silicon dioxide, compressible sugar, corn starch, magnesium stearate, and microcrystalline cellulose.

The 5 mg also contains D&C yellow no. 10 aluminum lake and FD&C red no. 40 aluminum lake.

The 10 mg also contains FD&C red no. 40 aluminum lake and FD&C yellow no. 6 aluminum lake.

CLINICAL PHARMACOLOGY

Amphetamines are non-catecholamine, sympathomimetic amines with CNS stimulant activity. Peripheral actions include elevations of systolic and diastolic blood pressures and weak bronchodilator and respiratory stimulant action.

There is neither specific evidence which clearly establishes the mechanism whereby amphetamines produce mental and behavioral effects in children, nor conclusive evidence regarding how these effects relate to the condition of the central nervous system.

Pharmacokinetics

The pharmacokinetics of the tablet and sustained-release capsule were compared in 12 healthy subjects. The extent of bioavailability of the sustained-release capsule was similar compared to the immediate-release tablet. Following administration of three 5 mg tablets, average maximal dextroamphetamine plasma concentrations (Cmax) of 36.6 ng/mL were achieved at approximately 3 hours. Following administration of one 15 mg sustained-release capsule, maximal dextroamphetamine plasma concentrations were obtained approximately 8 hours after dosing. The average Cmax was 23.5 ng/mL. The average plasma T1/2 was similar for both the tablet and sustained-release capsule and was approximately 12 hours.

In 12 healthy subjects, the rate and extent of dextroamphetamine absorption were similar following administration of the sustained-release capsule formulation in the fed (58 to 75 gm fat) and fasted state.

INDICATIONS AND USAGE

Dextroamphetamine Sulfate Tablets USP are indicated for:

1. Narcolepsy.
2. Attention Deficit Disorder with Hyperactivity, as an integral part of a total treatment program which typically includes other remedial measures (psychological, educational, social) for a stabilizing effect in pediatric patients (ages 3 to 16 years) with a behavioral syndrome characterized by the following group of developmentally inappropriate symptoms: moderate to severe distractibility, short attention span, hyperactivity, emotional lability, and impulsivity. The diagnosis of this syndrome should not be made with finality when these symptoms are only of comparatively recent origin. Nonlocalizing (soft) neurological signs, learning disability, and abnormal EEG may or may not be present, and a diagnosis of central nervous system dysfunction may or may not be warranted.

CONTRAINDICATIONS

Advanced arteriosclerosis, symptomatic cardiovascular disease, moderate to severe hypertension, hyperthyroidism, known hypersensitivity or idiosyncrasy to the sympathomimetic amines, glaucoma.

Agitated states.

Patients with a history of drug abuse.

During or within 14 days following the administration of monoamine oxidase inhibitors (hypertensive crises may result).

WARNINGS

Serious Cardiovascular Events

Sudden Death in Patients with Pre-existing Structural Cardiac Abnormalities or Other Serious Heart Problems

Children and Adolescents

Sudden death has been reported in association with CNS stimulant treatment at usual doses in children and adolescents with structural cardiac abnormalities or other serious heart problems. Although some serious heart problems alone carry an increased risk of sudden death, stimulant products generally should not be used in children or adolescents with known serious structural cardiac abnormalities, cardiomyopathy, serious heart rhythm abnormalities, or other serious cardiac problems that may place them at increased vulnerability to the sympathomimetic effects of a stimulant drug.

Adults

Sudden deaths, stroke, and myocardial infarction have been reported in adults taking stimulant drugs at usual doses for ADHD. Although the role of stimulants in these adult cases is also unknown, adults have a greater likelihood than children of having serious structural cardiac abnormalities, cardiomyopathy, serious heart rhythm abnormalities, coronary artery disease, or other serious cardiac problems. Adults with such abnormalities should also generally not be treated with stimulant drugs (see CONTRAINDICATIONS).

Hypertension and Other Cardiovascular Conditions

Stimulant medications cause a modest increase in average blood pressure (about 2-4 mmHg) and average heart rate (about 3-6 bpm), and individuals may have larger increases. While the mean changes alone would not be expected to have short-term consequences, all patients should be monitored for larger changes in heart rate and blood pressure. Caution is indicated in treating patients whose underlying medical conditions might be compromised by increases in blood pressure or heart rate, e.g., those with pre-existing hypertension, heart failure, recent myocardial infarction, or ventricular arrhythmia (see CONTRAINDICATIONS).

Assessing Cardiovascular Status in Patients Being Treated With Stimulant Medications

Children, adolescents, or adults who are being considered for treatment with stimulant medications should have a careful history (including assessment for a family history of sudden death or ventricular arrhythmia) and physical exam to assess for the presence of cardiac disease, and should receive further cardiac evaluation if findings suggest such disease (e.g., electrocardiogram and echocardiogram). Patients who develop symptoms such as exertional chest pain, unexplained syncope, or other symptoms suggestive of cardiac disease during stimulant treatment should undergo a prompt cardiac evaluation.

Psychiatric Adverse Events

Pre-Existing Psychosis

Administration of stimulants may exacerbate symptoms of behavior disturbance and thought disorder in patients with a pre-existing psychotic disorder.

Bipolar Illness

Particular care should be taken in using stimulants to treat ADHD in patients with comorbid bipolar disorder because of concern for possible induction of a mixed/manic episode in such patients. Prior to initiating treatment with a stimulant, patients with comorbid depressive symptoms should be adequately screened to determine if they are at risk for bipolar disorder; such screening should include a detailed psychiatric history, including a family history of suicide, bipolar disorder, and depression.

Emergence of New Psychotic or Manic Symptoms

Treatment emergent psychotic or manic symptoms, e.g., hallucinations, delusional thinking, or mania in children and adolescents without a prior history of psychotic illness or mania can be caused by stimulants at usual doses. If such symptoms occur, consideration should be given to a possible causal role of the stimulant, and discontinuation of treatment may be appropriate. In a pooled analysis of multiple short-term, placebo-controlled studies, such symptoms occurred in about 0.1% (4 patients with events out of 3,482 exposed to methylphenidate or amphetamine for several weeks at usual doses) of stimulant-treated patients compared to 0 in placebo-treated patients.

Aggression

Aggressive behavior or hostility is often observed in children and adolescents with ADHD, and has been reported in clinical trials and the postmarketing experience of some medications indicated for the treatment of ADHD. Although there is no systematic evidence that stimulants cause aggressive behavior or hostility, patients beginning treatment for ADHD should be monitored for the appearance of, or worsening of, aggressive behavior or hostility.

Long-Term Suppression of Growth

Careful follow-up of weight and height in children ages 7 to 10 years who were randomized to either methylphenidate or non-medication treatment groups over 14 months, as well as in naturalistic subgroups of newly methylphenidate-treated and non-medication treated children over 36 months (to the ages of 10 to 13 years), suggests that consistently medicated children (i.e., treatment for 7 days per week throughout the year) have a temporary slowing in growth rate (on average, a total of about 2 cm less growth in height and 2.7 kg less growth in weight over 3 years), without evidence of growth rebound during this period of development. Published data are inadequate to determine whether chronic use of amphetamines may cause a similar suppression of growth, however, it is anticipated that they likely have this effect as well. Therefore, growth should be monitored during treatment with stimulants, and patients who are not growing or gaining height or weight as expected may need to have their treatment interrupted.

Seizures

There is some clinical evidence that stimulants may lower the convulsive threshold in patients with prior history of seizures, in patients with prior EEG abnormalities in absence of seizures, and, very rarely, in patients without a history of seizures and no prior EEG evidence of seizures. In the presence of seizures, the drug should be discontinued.

Peripheral Vasculopathy, Including Raynaud's Phenomenon

Stimulants, including dextroamphetamine sulfate tablets, used to treat ADHD are associated with peripheral vasculopathy, including Raynaud's phenomenon. Signs and symptoms are usually intermittent and mild; however, very rare sequelae include digital ulcerations and/or soft tissue breakdown. Effects of peripheral vasculopathy, including Raynaud's phenomenon, were observed in post-marketing reports at different times and at therapeutic doses in all age groups throughout the course of treatment. Signs and symptoms generally improve after reduction in dose or discontinuation of drug. Careful observation for digital changes is necessary during treatment with ADHD stimulants. Further clinical evaluation (e.g., rheumatology referral) may be appropriate for certain patients.

Serotonin Syndrome

Serotonin Syndrome, a potentially life-threatening reaction, may occur when amphetamines are used in combination with other drugs that affect the serotonergic neurotransmitter systems such as monoamine oxidase inhibitors (MAOIs), selective serotonin reuptake inhibitors (SSRIs), serotonin norepinephrine reuptake inhibitors (SNRIs), triptans, tricyclic antidepressants, fentanyl, lithium, tramadol, tryptophan, buspirone, and St. John's Wort [see DRUG INTERACTIONS]. Amphetamines and amphetamine derivatives are known to be metabolized, to some degree, by cytochrome P450 2D6 (CYP2D6) and display minor inhibition of CYP2D6 metabolism [see CLINICAL PHARMACOLOGY]. The potential for a pharmacokinetic interaction exists with the co-administration of CYP2D6 inhibitors which may increase the risk with increased exposure to dextroamphetamine sulfate tablets. In these situations, consider an alternative non-serotonergic drug or an alternative drug that does not inhibit CYP2D6 [see DRUG INTERACTIONS].

Serotonin syndrome symptoms may include mental status changes (e.g., agitation, hallucinations, delirium, and coma), autonomic instability (e.g., tachycardia, labile blood pressure, dizziness, diaphoresis, flushing, hyperthermia), neuromuscular symptoms (e.g., tremor, rigidity, myoclonus, hyperreflexia, incoordination), seizures, and/or gastrointestinal symptoms (e.g., nausea, vomiting, diarrhea).

Concomitant use of dextroamphetamine sulfate tablets with MAOI drugs is contraindicated [see CONTRAINDICATIONS].

Discontinue treatment with dextroamphetamine sulfate tablets and any concomitant serotonergic agents immediately if the above symptoms occur, and initiate supportive symptomatic treatment. If concomitant use of dextroamphetamine sulfate tablets with other serotonergic drugs or CYP2D6 inhibitors is clinically warranted, initiate dextroamphetamine sulfate tablets with lower doses, monitor patients for the emergence of serotonin syndrome during drug initiation or titration, and inform patients of the increased risk for serotonin syndrome.

Visual Disturbance

Difficulties with accommodation and blurring of vision have been reported with stimulant treatment.

PRECAUTIONS

General

The least amount feasible should be prescribed or dispensed at one time in order to minimize the possibility of overdosage.

Information for Patients

Amphetamines may impair the ability of the patient to engage in potentially hazardous activities such as operating machinery or vehicles; the patient should therefore be cautioned accordingly.

Prescribers or other health professionals should inform patients, their families, and their caregivers about the benefits and risks associated with treatment with dextroamphetamine and should counsel them in its appropriate use. A patient Medication Guide is available for dextroamphetamine. The prescriber or health professional should instruct patients, their families, and their caregivers to read the Medication Guide and should assist them in understanding its contents. Patients should be given the opportunity to discuss the contents of the Medication Guide and to obtain answers to any questions they may have. The complete text of the Medication Guide is reprinted at the end of this document.

Circulation problems in fingers and toes [Peripheral vasculopathy, including Raynaud's phenomenon]

- Instruct patients beginning treatment with dextroamphetamine sulfate tablets about the risk of peripheral vasculopathy, including Raynaud's Phenomenon, and associated signs and symptoms: fingers or toes may feel numb, cool, painful, and/or may change color from pale, to blue, to red.
- Instruct patients to report to their physician any new numbness, pain, skin color change, or sensitivity to temperature in fingers or toes.
- Instruct patients to call their physician immediately with any signs of unexplained wounds appearing on fingers or toes while taking dextroamphetamine sulfate tablets.
- Further clinical evaluation (e.g., rheumatology referral) may be appropriate for certain patients.

Drug Interactions

Acidifying Agents

Gastrointestinal acidifying agents (guanethidine, reserpine, glutamic acid HCl, ascorbic acid, fruit juices, etc.) lower absorption of amphetamines. Urinary acidifying agents (ammonium chloride, sodium acid phosphate, etc.) increase the concentration of the ionized species of the amphetamine molecule, thereby increasing urinary excretion. Both groups of agents lower blood levels and efficacy of amphetamines.

Adrenergic Blockers

Adrenergic blockers are inhibited by amphetamines.

Alkalinizing Agent

Gastrointestinal alkalinizing agents (sodium bicarbonate, etc.) increase absorption of amphetamines. Urinary alkalinizing agents (acetazolamide, some thiazides) increase the concentration of the non-ionized species of the amphetamine molecule, thereby decreasing urinary excretion. Both groups of agents increase blood levels and therefore potentiate the actions of amphetamines.

Antidepressants, Tricyclic

Amphetamines may enhance the activity of tricyclic or sympathomimetic agents; d-amphetamine with desipramine or protriptyline and possibly other tricyclics cause striking and sustained increases in the concentration of d-amphetamine in the brain; cardiovascular effects can be potentiated.

CYP2D6 Inhibitors

The concomitant use of dextroamphetamine sulfate tablets and CYP2D6 inhibitors may increase the exposure of dextroamphetamine sulfate tablets compared to the use of the drug alone and increase the risk of serotonin syndrome. Initiate with lower doses and monitor patients for signs and symptoms of serotonin syndrome particularly during dextroamphetamine sulfate tablets initiation and after a dosage increase. If serotonin syndrome occurs, discontinue dextroamphetamine sulfate tablets and the CYP2D6 inhibitor [see WARNINGS, OVERDOSAGE]. Examples of CYP2D6 Inhibitors include paroxetine and fluoxetine (also serotonergic drugs), quinidine, ritonavir.

Serotonergic Drugs

The concomitant use of dextroamphetamine sulfate tablets and serotonergic drugs increases the risk of serotonin syndrome. Initiate with lower doses and monitor patients for signs and symptoms of serotonin syndrome, particularly during dextroamphetamine sulfate tablets initiation or dosage increase. If serotonin syndrome occurs, discontinue dextroamphetamine sulfate tablets and the concomitant serotonergic drug(s) [see WARNINGS and PRECAUTIONS]. Examples of serotonergic drugs include selective serotonin reuptake inhibitors (SSRI), serotonin norepinephrine reuptake inhibitors (SNRI), triptans, tricyclic antidepressants, fentanyl, lithium, tramadol, tryptophan, buspirone, St. John's Wort.

MAO Inhibitors

MAOI antidepressants, as well as a metabolite of furazolidone, slow amphetamine metabolism. This slowing potentiates amphetamines, increasing their effect on the release of norepinephrine and other monoamines from adrenergic nerve endings; this can cause headaches and other signs of hypertensive crisis. A variety of neurological toxic effects and malignant hyperpyrexia can occur, sometimes with fatal results.

Antihistamines

Amphetamines may counteract the sedative effect of antihistamines.

Antihypertensives

Amphetamines may antagonize the hypotensive effects of antihypertensives.

Chlorpromazine

Chlorpromazine blocks dopamine and norepinephrine reuptake, thus inhibiting the central stimulant effects of amphetamines, and can be used to treat amphetamine poisoning.

Ethosuximide

Amphetamines may delay intestinal absorption of ethosuximide.

Haloperidol

Haloperidol blocks dopamine and norepinephrine reuptake, thus inhibiting the central stimulant effects of amphetamines.

Lithium Carbonate

The stimulatory effects of amphetamines may be inhibited by lithium carbonate.

Meperidine

Amphetamines potentiate the analgesic effect of meperidine.

Methenamine Therapy

Urinary excretion of amphetamines is increased, and efficacy is reduced, by acidifying agents used in methenamine therapy.

Norepinephrine

Amphetamines enhance the adrenergic effect of norepinephrine.

Phenobarbital

Amphetamines may delay intestinal absorption of phenobarbital; co-administration of phenobarbital may produce a synergistic anticonvulsant action.

Phenytoin

Amphetamines may delay intestinal absorption of phenytoin; co-administration of phenytoin may produce a synergistic anticonvulsant action.

Propoxyphene

In cases of propoxyphene overdosage, amphetamine CNS stimulation is potentiated and fatal convulsions can occur.

Veratrum Alkaloids

Amphetamines inhibit the hypotensive effect of veratrum alkaloids.

Drug/Laboratory Test Interactions

- Amphetamines can cause a significant elevation in plasma corticosteroid levels. This increase is greatest in the evening.
- Amphetamines may interfere with urinary steroid determinations.

Carcinogenesis/Mutagenesis

Mutagenicity studies and long-term studies in animals to determine the carcinogenic potential of dextroamphetamine sulfate have not been performed.

Pregnancy

Teratogenic Effects

Pregnancy Category C

Dextroamphetamine has been shown to have embryotoxic and teratogenic effects when administered to A/Jax mice and C57BL mice in doses approximately 41 times the maximum human dose. Embryotoxic effects were not seen in New Zealand white rabbits given the drug in doses 7 times the human dose nor in rats given 12.5 times the maximum human dose. While there are no adequate and well-controlled studies in pregnant women, there has been one report of severe congenital bony deformity, tracheoesophageal fistula, and anal atresia (Vater association) in a baby born to a woman who took dextroamphetamine sulfate with lovastatin during the first trimester of pregnancy. Dextroamphetamine should be used during pregnancy only if the potential benefit justifies the potential risk to the fetus.

Nonteratogenic Effects

Infants born to mothers dependent on amphetamines have an increased risk of premature delivery and low birth weight. Also, these infants may experience symptoms of withdrawal as demonstrated by dysphoria, including agitation, and significant lassitude.

Nursing Mothers

Amphetamines are excreted in human milk. Mothers taking amphetamines should be advised to refrain from nursing.

Pediatric Use

Long-term effects of amphetamines in pediatric patients have not been well established.

Amphetamines are not recommended for use in pediatric patients under 3 years of age with Attention Deficit Disorder with Hyperactivity described under INDICATIONS AND USAGE.

Clinical experience suggests that in psychotic pediatric patients, administration of amphetamines may exacerbate symptoms of behavior disturbance and thought disorder.

Amphetamines have been reported to exacerbate motor and phonic tics and Tourette's syndrome. Therefore, clinical evaluation for tics and Tourette's syndrome in pediatric patients and their families should precede use of stimulant medications.

Data are inadequate to determine whether chronic administration of amphetamines may be associated with growth inhibition; therefore, growth should be monitored during treatment.

Drug treatment is not indicated in all cases of Attention Deficit Disorder with Hyperactivity and should be considered only in light of the complete history and evaluation of the pediatric patient. The decision to prescribe amphetamines should depend on the physician's assessment of the chronicity and severity of the pediatric patient's symptoms and their appropriateness for his/her age. Prescription should not depend solely on the presence of one or more of the behavioral characteristics.

When these symptoms are associated with acute stress reactions, treatment with amphetamines is usually not indicated.

ADVERSE REACTIONS

Cardiovascular

Palpitations, tachycardia, elevation of blood pressure. There have been isolated reports of cardiomyopathy associated with chronic amphetamine use.

Central Nervous System

Psychotic episodes at recommended doses (rare), overstimulation, restlessness, dizziness, insomnia, euphoria, dyskinesia, dysphoria, tremor, headache, exacerbation of motor and phonic tics and Tourette's syndrome.

Gastrointestinal

Dryness of the mouth, unpleasant taste, diarrhea, constipation, intestinal ischemia and other gastrointestinal disturbances. Anorexia and weight loss may occur as undesirable effects.

Allergic

Urticaria.

Endocrine

Impotence, changes in libido, frequent or prolonged erections.

Musculoskeletal

Rhabdomyolysis

DRUG ABUSE AND DEPENDENCE

Dextroamphetamine sulfate is a Schedule II controlled substance.

Amphetamines have been extensively abused. Tolerance, extreme psychological dependence and severe social disability have occurred. There are reports of patients who have increased the dosage to many times that recommended. Abrupt cessation following prolonged high dosage administration results in extreme fatigue and mental depression; changes are also noted on the sleep EEG.

Manifestations of chronic intoxication with amphetamines include severe dermatoses, marked insomnia, irritability, hyperactivity and personality changes. The most severe manifestation of chronic intoxication is psychosis, often clinically indistinguishable from schizophrenia. This is rare with oral amphetamines.

OVERDOSAGE

Individual patient response to amphetamines varies widely. While toxic symptoms occasionally occur as an idiosyncrasy at doses as low as 2 mg, they are rare with doses of less than 15 mg; 30 mg can produce severe reactions, yet doses of 400 to 500 mg are not necessarily fatal.

In rats, the oral LD50 of dextroamphetamine sulfate is 96.8 mg/kg.

Manifestations of acute overdosage with amphetamines include restlessness, tremor, hyperreflexia, rhabdomyolysis, rapid respiration, hyperpyrexia, confusion, assaultiveness, hallucinations, panic states.

Fatigue and depression usually follow the central stimulation.

Cardiovascular effects include arrhythmias, hypertension or hypotension and circulatory collapse. Gastrointestinal symptoms include nausea, vomiting, diarrhea and abdominal cramps. Fatal poisoning is usually preceded by convulsions and coma.

Treatment

Consult with a Certified Poison Control Center for up-to-date guidance and advice. Management of acute amphetamine intoxication is largely symptomatic and includes gastric lavage, administration of activated charcoal, administration of a cathartic, and sedation. Experience with hemodialysis or peritoneal dialysis is inadequate to permit recommendation in this regard. Acidification of the urine increases amphetamine excretion, but is believed to increase risk of acute renal failure if myoglobinuria is present. If acute, severe hypertension complicates amphetamine overdosage, administration of intravenous phentolamine has been suggested. However, a gradual drop in blood pressure will usually result when sufficient sedation has been achieved.

Chlorpromazine antagonizes the central stimulant effects of amphetamines and can be used to treat amphetamine intoxication.

DOSAGE AND ADMINISTRATION

Amphetamines should be administered at the lowest effective dosage and dosage should be individually adjusted. Late evening doses should be avoided because of the resulting insomnia.

Narcolepsy

Usual dose is 5 to 60 mg per day in divided doses, depending on the individual patient response.

Narcolepsy seldom occurs in children under 12 years of age; however, when it does, dextroamphetamine sulfate may be used. The suggested initial dose for patients aged 6 to 12 is 5 mg daily; daily dose may be raised in increments of 5 mg at weekly intervals until an optimal response is obtained. In patients 12 years of age and older, start with 10 mg daily; daily dosage may be raised in increments of 10 mg at weekly intervals until optimal response is obtained. If bothersome adverse reactions appear (e.g., insomnia or anorexia), dosage should be reduced. Give first dose on awakening; additional doses (1 or 2) at intervals of 4 to 6 hours.

Attention Deficit Disorder with Hyperactivity

Not recommended for pediatric patients under 3 years of age.

In pediatric patients from 3 to 5 years of age, start with 2.5 mg daily; daily dosage may be raised in increments of 2.5 mg at weekly intervals until optimal response is obtained.

In pediatric patients 6 years of age and older, start with 5 mg once or twice daily; daily dosage may be raised in increments of 5 mg at weekly intervals until optimal response is obtained. Only in rare cases will it be necessary to exceed a total of 40 mg per day.

Give first dose on awakening; additional doses (1 or 2) at intervals of 4 to 6 hours.

Where possible, drug administration should be interrupted occasionally to determine if there is a recurrence of behavioral symptoms sufficient to require continued therapy.

HOW SUPPLIED

Dextroamphetamine Sulfate Tablets USP are available as:

5 mg: Peach, round, flat-faced, bevel edged, scored tablet, debossed "N" score "941" on one side and plain on the other side.

NDC 68382-941-01……….Bottles of 100 Tablets

10 mg: Pink, round, flat-faced, bevel edged, scored tablet, debossed "N" score "942" on one side and plain on the other side.

NDC 68382-942-01……….Bottles of 100 Tablets

Dispense in a tight, light-resistant container as defined in the USP, with a child-resistant closure (as required).

Store at 20º to 25ºC (68º to 77ºF) [See USP Controlled Room Temperature].

KEEP THIS AND ALL MEDICATIONS OUT OF THE REACH OF CHILDREN.

DEA Order Form Required.

Manufactured By:

Nesher Pharmaceuticals USA LLC

St. Louis, MO 63044

Distributed by:

Zydus Pharmaceuticals USA Inc.

Pennington, NJ 08534

P10138-4 12/2021

MEDICATION GUIDE

DEXTROAMPHETAMINE SULFATE TABLETS USP, CII

(DEX-troe-am-FET-uh-meen SULL-fate)

Read the Medication Guide that comes with Dextroamphetamine Sulfate Tablets before you or your child starts taking them and each time you get a refill. There may be new information. This Medication Guide does not take the place of talking to your doctor about you or your child's treatment with Dextroamphetamine Sulfate Tablets.

BOXED WARNING

What is the most important information I should know about Dextroamphetamine Sulfate Tablets?

The following have been reported with use of Dextroamphetamine Sulfate Tablets and other stimulant medicines.

1. Heart-related problems:

- sudden death in patients who have heart problems or heart defects
- stroke and heart attack in adults
- increased blood pressure and heart rate

Tell your doctor if you or your child have any heart problems, heart defects, high blood pressure, or a family history of these problems.

Your doctor should check you or your child carefully for heart problems before starting Dextroamphetamine Sulfate Tablets.

Your doctor should check your or your child's blood pressure and heart rate regularly during treatment with Dextroamphetamine Sulfate Tablets.

Call your doctor right away if you or your child has any signs of heart problems such as chest pain, shortness of breath, or fainting while taking Dextroamphetamine Sulfate Tablets.

2. Mental (Psychiatric) problems:

All Patients

- new or worse behavior and thought problems
- new or worse bipolar illness
- new or worse aggressive behavior or hostility

Children and Teenagers

- new psychotic symptoms (such as hearing voices, believing things that are not true, are suspicious) or new manic symptoms

Tell your doctor about any mental problems you or your child have, or about a family history of suicide, bipolar illness, or depression.

Call your doctor right away if you or your child have any new or worsening mental symptoms or problems while taking Dextroamphetamine Sulfate Tablets, especially seeing or hearing things that are not real, believing things that are not real, or are suspicious.

3. Circulation problems in fingers and toes [Peripheral vasculopathy, including Raynaud's phenomenon]:

- Fingers or toes may feel numb, cool, painful
- Fingers or toes may change color from pale, to blue, to red

Tell your doctor if you have or your child has numbness, pain, skin color change, or sensitivity to temperature in your fingers or toes.

Call your doctor right away if you have or your child has any signs of unexplained wounds appearing on fingers or toes while taking Dextroamphetamine Sulfate Tablets.

Dextroamphetamine Sulfate Tablets may not be right for you or your child. Before starting Dextroamphetamine Sulfate Tablets tell your or your child's doctor about all health conditions (or a family history of) including:

- circulation problems in fingers and toes.

What are Dextroamphetamine Sulfate Tablets?

Dextroamphetamine Sulfate Tablets are a central nervous system stimulant prescription medicine. It is used for the treatment of Attention Deficit Hyperactivity Disorder (ADHD). Dextroamphetamine Sulfate Tablets may help increase attention and decrease impulsiveness and hyperactivity in patients with ADHD.

Dextroamphetamine Sulfate Tablets should be used as a part of a total treatment program for ADHD that may include counseling or other therapies.

Dextroamphetamine Sulfate Tablets are also used in the treatment of a sleep disorder called narcolepsy.

BOXED WARNING

Dextroamphetamine Sulfate is a federally controlled substance (CII) because it can be abused or lead to dependence. Keep Dextroamphetamine Sulfate Tablets in a safe place to prevent misuse and abuse. Selling or giving away Dextroamphetamine Sulfate Tablets may harm others, and is against the law.

Tell your doctor if you or your child have (or have a family history of) ever abused or been dependent on alcohol, prescription medicines or street drugs.

Who should not take Dextroamphetamine Sulfate Tablets?

Dextroamphetamine Sulfate Tablets should not be taken if you or your child:

- have heart disease or hardening of the arteries
- have moderate to severe high blood pressure
- have hyperthyroidism
- have an eye problem called glaucoma
- are very anxious, tense, or agitated
- have a history of drug abuse
- are taking or have taken within the past 14 days an anti-depression medicine called a monoamine oxidase inhibitor or MAOI.
- is sensitive to, allergic to, or had a reaction to other stimulant medicines

Dextroamphetamine Sulfate Tablets are not recommended for use in children less than 3 years old.

Dextroamphetamine Sulfate Tablets may not be right for you or your child. Before starting Dextroamphetamine Sulfate Tablets tell your or your child's doctor about all health conditions (or a family history of) including:

- heart problems, heart defects, high blood pressure
- mental problems including psychosis, mania, bipolar illness, or depression
- tics or Tourette's syndrome
- thyroid problems
- seizures or have had an abnormal brain wave test (EEG)

Tell your doctor if you or your child is pregnant, planning to become pregnant, or breastfeeding.

Can Dextroamphetamine Sulfate Tablets be taken with other medicines?

Tell your doctor about all of the medicines that you or your child take including prescription and non-prescription medicines, vitamins, and herbal supplements.

Dextroamphetamine Sulfate Tablets and some medicines may interact with each other and cause serious side effects. Sometimes the doses of other medicines will need to be adjusted while taking Dextroamphetamine Sulfate Tablets.

Your doctor will decide whether Dextroamphetamine Sulfate Tablets can be taken with other medicines.

Especially tell your doctor if you or your child take:

- anti-depression medicines including MAOIs
- blood pressure medicines
- antacids
- seizure medicines

Know the medicines that you or your child take. Keep a list of your medicines with you to show your doctor and pharmacist.

Do not start any new medicine while taking Dextroamphetamine Sulfate Tablets without talking to your doctor first.

How should Dextroamphetamine Sulfate Tablets be taken?

- Take Dextroamphetamine Sulfate Tablets exactly as prescribed. Your doctor may adjust the dose until it is right for you or your child.
- Dextroamphetamine Sulfate Tablets are usually taken two or three times a day. The first dose is usually taken in the morning. One or two more doses may be taken during the day, 4 to 6 hours apart.
- From time to time, your doctor may stop Dextroamphetamine Sulfate Tablets treatment for a while to check ADHD symptoms.
- Your doctor may do regular checks of the blood, heart, and blood pressure while taking Dextroamphetamine Sulfate Tablets. Children should have their height and weight checked often while taking Dextroamphetamine Sulfate Tablets. Dextroamphetamine Sulfate Tablets treatment may be stopped if a problem is found during these check-ups.
- If you or your child take too much Dextroamphetamine Sulfate Tablets or overdoses, call your doctor or poison control center right away, or get emergency treatment.

What are possible side effects of Dextroamphetamine Sulfate Tablets?

See "What is the most important information I should know about Dextroamphetamine Sulfate Tablets?" for information on reported heart and mental problems.

Other serious side effects include:

- slowing of growth (height and weight) in children
- seizures, mainly in patients with a history of seizures
- eyesight changes or blurred vision
- Serotonin syndrome. A potentially life-threatening problem called serotonin syndrome can happen when medicines such as dextroamphetamine sulfate tablets are taken with certain other medicines. Symptoms of serotonin syndrome may include:
  - agitation, hallucinations, coma or other changes in mental status
  - problems controlling your movements or muscle twitching
  - fast heartbeat
  - high or low blood pressure
  - sweating or fever
  - nausea or vomiting
  - diarrhea
  - muscle stiffness or tightness

Common side effects include:

- fast heart beat
- decreased appetite
- tremors
- headache
- trouble sleeping
- dizziness
- stomach upset
- weight loss
- dry mouth

Dextroamphetamine Sulfate Tablets may affect your or your child's ability to drive or do other dangerous activities.

Talk to your doctor if you or your child have side effects that are bothersome or do not go away.

This is not a complete list of possible side effects. Ask your doctor or pharmacist for more information.

Call your doctor for medical advice about side effects. You may report side effects to FDA at 1-800-FDA-1088.

How should I store Dextroamphetamine Sulfate Tablets?

- Store Dextroamphetamine Sulfate Tablets in a safe place at room temperature, 20° to 25°C (68° to 77°F).
- Keep Dextroamphetamine Sulfate Tablets and all medicines out of the reach of children.

General information about Dextroamphetamine Sulfate Tablets

Medicines are sometimes prescribed for purposes other than those listed in a Medication Guide. Do not use Dextroamphetamine Sulfate Tablets for a condition for which they were not prescribed. Do not give Dextroamphetamine Sulfate Tablets to other people, even if they have the same condition. It may harm them and it is against the law. This Medication Guide summarizes the most important information about Dextroamphetamine Sulfate Tablets. If you would like more information, talk with your doctor. You can ask your doctor or pharmacist for information about Dextroamphetamine Sulfate Tablets that was written for healthcare professionals. For more information about Dextroamphetamine Sulfate Tablets, please contact Nesher Pharmaceuticals (USA) LLC at 1-314-209-4700.

What are the ingredients in Dextroamphetamine Sulfate Tablets?

Active Ingredient: dextroamphetamine sulfate

Inactive Ingredients

Calcium sulfate, colloidal silicon dioxide, compressible sugar, corn starch, magnesium stearate, and microcrystalline cellulose.

The 5 mg also contains D&C yellow no. 10 aluminum lake and FD&C red no. 40 aluminum lake.

The 10 mg also contains FD&C red no. 40 aluminum lake and FD&C yellow no. 6 aluminum lake.

This Medication Guide has been approved by the U.S. Food and Drug Administration.

Manufactured By:

Nesher Pharmaceuticals USA LLC

St. Louis, MO 63044

Distributed by:

Zydus Pharmaceuticals USA Inc.

Pennington, NJ 08534

P10138-4 12/2021

PRINCIPAL DISPLAY PANEL - Bottle Label 5 mg

ZyGenerics

NDC 68382-941-01

Dextroamphetamine Sulfate CII

Tablets, USP

5 mg

PHARMACIST: DISPENSE THE ACCOMPANYING MEDICATION GUIDE TO EACH PATIENT

Rx only

100 Tablets

PRINCIPAL DISPLAY PANEL - Bottle Label 10 mg

ZyGenerics

NDC 68382-942-01

Dextroamphetamine Sulfate CII

Tablets, USP

10 mg

PHARMACIST: DISPENSE THE ACCOMPANYING MEDICATION GUIDE TO EACH PATIENT

Rx only

100 Tablets